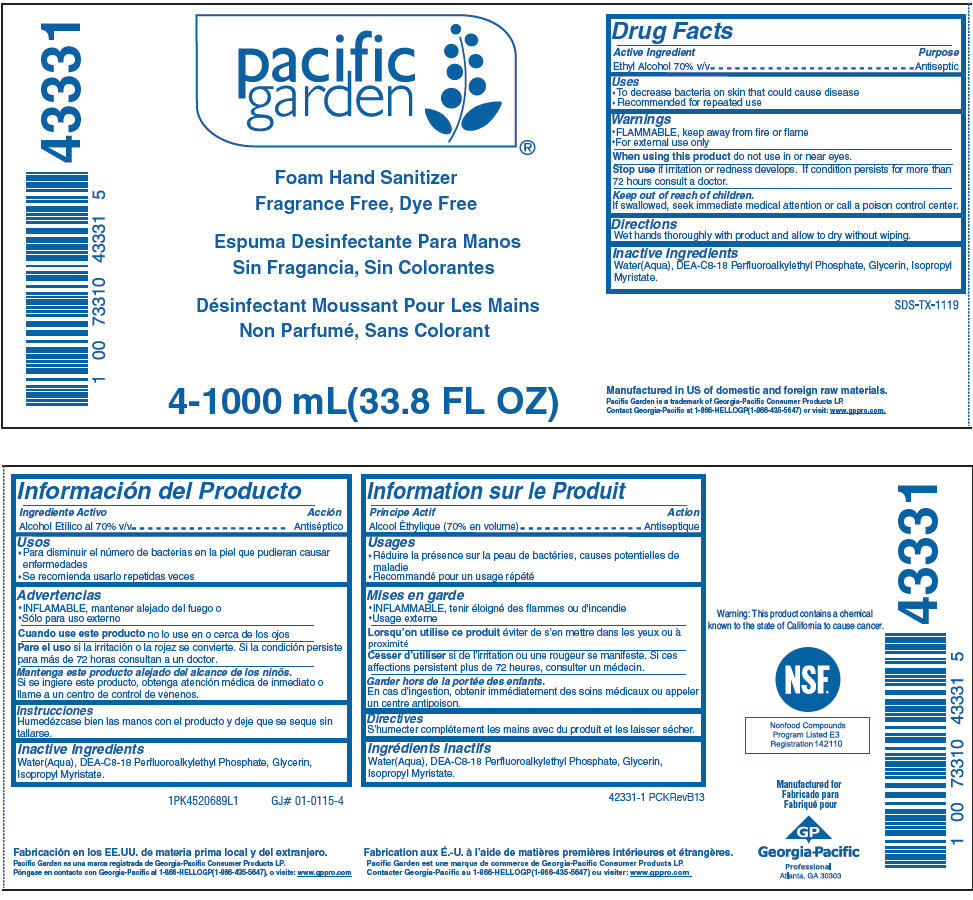 DRUG LABEL: Pacific Garden Foam Hand Sanitizer, Fragrance Free, Dye Free
NDC: 54622-689 | Form: SOAP
Manufacturer: Georgia-Pacific Consumer Products LP
Category: otc | Type: HUMAN OTC DRUG LABEL
Date: 20180125

ACTIVE INGREDIENTS: ALCOHOL 0.7 mL/1 mL
INACTIVE INGREDIENTS: WATER; DIETHANOLAMINE BIS(C8-C18 PERFLUOROALKYLETHYL)PHOSPHATE; GLYCERIN; ISOPROPYL MYRISTATE

Pacific Garden Foam Hand Sanitizer, Fragrance Free, Dye Free

Drug Facts

Active Ingredient

Ethyl Alcohol 70% (v/v)

Purpose

Antimicrobial

Uses

- To decrease bacteria on skin that could cause disease.
- Recommended for repeated use.

Warnings

- FLAMMABLE, keep away from fire or flame
- For external use only

When using this product do not use in or near eyes.

Stop use if irritation or redness develops. If condition persists for more than 72 hours consult a doctor.

Keep out of reach of children.

If swallowed, seek immediate medical attention or call a poison control center.

Directions

- Wet hands thoroughly with product and allow to dry without wiping.

Inactive ingredients

- Water/Aqua, DEA-C8-18 Perfluoroalkylethyl Phosphate, Glycerin, Isopropyl Myristate

Warning: This product contains a chemical known to the state of California to cause cancer.

PRINCIPAL DISPLAY PANEL - 1000 mL Bottle Label

pacific
garden

Foam Hand Sanitizer
Fragrance Free, Dye Free

4-1000 mL(33.8 FL OZ)